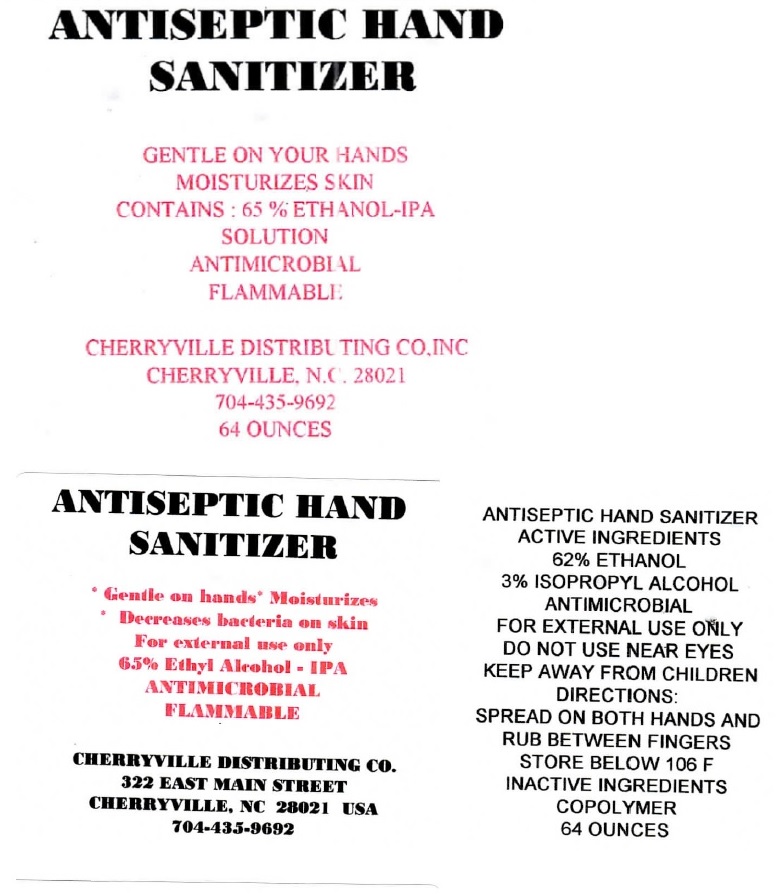 DRUG LABEL: ANTISEPTIC HAND SANITIZER
NDC: 90006-023 | Form: SOLUTION
Manufacturer: Cherryville Distributing Company, Inc.
Category: otc | Type: HUMAN OTC DRUG LABEL
Date: 20200824

ACTIVE INGREDIENTS: ALCOHOL 62 mL/100 mL
INACTIVE INGREDIENTS: ISOPROPYL ALCOHOL; METHACRYLIC ACID - ETHYL ACRYLATE COPOLYMER (4500 MPA.S)

ANTISEPTIC HAND SANITIZER

ACTIVE INGREDIENTS

62% ETHANOL

PURPOSE

ANTIMICROBIAL

USES

Decreases bacteria on skin

WARNINGS

FOR EXTERNAL USE ONLY

DO NOT USE NEAR EYES

FLAMMABLE

KEEP AWAY FROM CHILDREN

DIRECTIONS

SPREAD ON BOTH HANDS AND RUB BETWEEN FINGERS

STORAGE AND HANDLING

STORE BELOW 106 F

INACTIVE INGREDIENTS

ISOPROPYL ALCOHOL, COPOLYMER

*Gentle on hands* Moisturizes

CHERRYVILLE DISTRIBUTING CO.

322 EAST MAIN STREET

CHERRYVILLE, NC 28021 USA

704-435-9692